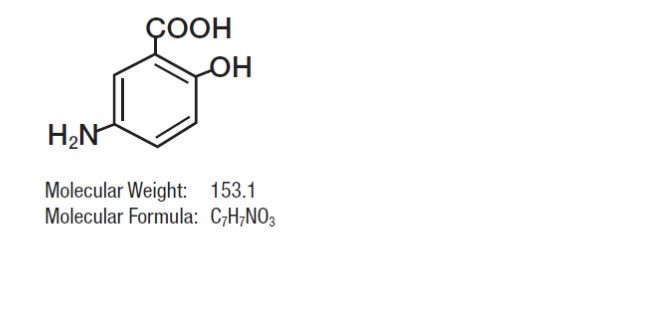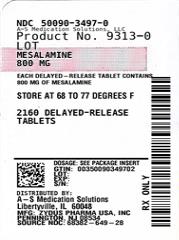 DRUG LABEL: mesalamine
NDC: 50090-3497 | Form: TABLET, DELAYED RELEASE
Manufacturer: A-S Medication Solutions
Category: prescription | Type: HUMAN PRESCRIPTION DRUG LABEL
Date: 20210304

ACTIVE INGREDIENTS: MESALAMINE 800 mg/1 1
INACTIVE INGREDIENTS: DIBUTYL SEBACATE; FERRIC OXIDE RED; FERRIC OXIDE YELLOW; LACTOSE MONOHYDRATE; MAGNESIUM STEARATE; METHACRYLIC ACID - METHYL METHACRYLATE COPOLYMER (1:1); METHACRYLIC ACID - METHYL METHACRYLATE COPOLYMER (1:2); POLYETHYLENE GLYCOL, UNSPECIFIED; POVIDONE, UNSPECIFIED; SILICON DIOXIDE; SODIUM STARCH GLYCOLATE TYPE A POTATO; TALC

HIGHLIGHTS OF PRESCRIBING INFORMATION

These highlights do not include all the information needed to use MESALAMINE DELAYED-RELEASE TABLETS safely and effectively. See full prescribing information for MESALAMINE DELAYED-RELEASE TABLETS.
Mesalamine delayed-release tablets, for oral use
Initial U.S. Approval: 1987

1 INDICATIONS AND USAGE

Mesalamine delayed-release tablets is an aminosalicylate indicated for the treatment of moderately active ulcerative colitis in adults. (1)

Limitation of Use:

Safety and effectiveness of Mesalamine delayed-release tablets beyond 6 weeks have not been established (1)

2 DOSAGE AND ADMINISTRATION

Important Administration Instructions (2.1):

- Do not substitute one Mesalamine delayed-release 800 mg tablet for two mesalamine delayed-release 400 mg oral products (2.1)
- Evaluate renal function prior to initiation of Mesalamine delayed-release tablets (2.1, 5.1)
- Take on an empty stomach, at least 1 hour before and 2 hours after a meal
- Swallow whole; do not cut, break or chew the tablets.

Treatment of Moderately Active Ulcerative Colitis (2.2):

- Recommended dosage is 1600 mg (two 800 mg tablets) three times daily for 6 weeks.

3 DOSAGE FORMS AND STRENGTHS

Delayed-release tablets: 800 mg (3)

4 CONTRAINDICATIONS

Known or suspected hypersensitivity to salicylates or aminosalicylates or to any of the ingredients of Mesalamine delayed-release tablets (4, 5.3).

5 WARNINGS AND PRECAUTIONS

- Renal Impairment: Evaluate the risks and benefits in patients with known renal impairment or taking nephrotoxic drugs; monitor renal function (5.1, 7.1, 8.6, 13.2)
- Mesalamine-induced Acute Intolerance Syndrome: Symptoms may be difficult to distinguish from an ulcerative colitis exacerbation; monitor for worsening symptoms; discontinue if acute intolerance syndrome suspected (5.2)
- Hypersensitivity Reactions, including Myocarditis and Pericarditis: Evaluate patients immediately and discontinue if a hypersensitivity reaction is suspected (5.3)
- Hepatic Failure: Evaluate the risks and benefits in patients with known liver impairment (5.4)

6 ADVERSE REACTIONS

The most common adverse reactions (≥2%) are headache, nausea, nasopharyngitis, abdominal pain, and worsening of ulcerative colitis (6.1)

To report SUSPECTED ADVERSE REACTIONS, contact Allergan at 1-800-433-8871 or FDA at 1-800-FDA-1088 or www.fda.gov/medwatch

7 DRUG INTERACTIONS

- Nephrotoxic Agents including NSAIDs: Increased risk of nephrotoxicity; monitor for changes in renal function and mesalamine-related adverse reactions. (7.1)
- Azathioprine or 6-Mercaptopurine: Increased risk of blood disorders; monitor complete blood cell counts and platelet counts (7.2)

8 USE IN SPECIFIC POPULATIONS

Geriatric Patients: Increased risk of blood dyscrasias; monitor complete blood cell counts and platelet counts (8.5)

FULL PRESCRIBING INFORMATION

1 INDICATIONS AND USAGE

Mesalamine delayed-release tablets is indicated for the treatment of moderately active ulcerative colitis in adults.

Limitations of Use:

Safety and effectiveness of Mesalamine delayed-release tablets beyond 6 weeks have not been established.

2 DOSAGE AND ADMINISTRATION

2.1 Important Administration Instructions

- Do not substitute one Mesalamine delayed-release 800 tablet for two mesalamine delayed-release 400 mg oral products [see Clinical Pharmacology (12.3)].
- Evaluate renal function prior to initiation of Mesalamine delayed-release tablets.
- Take Mesalamine delayed-release tablets on an empty stomach, at least 1 hour before and 2 hours after a meal [see Clinical Pharmacology (12.3)] .
- Swallow Mesalamine delayed-release tablets whole. Do not cut, break or chew the tablets.
- Intact, partially intact, and/or tablet shells have been reported in the stool; Instruct patients to contact their physician if this occurs repeatedly.
- Protect Mesalamine delayed-release tablets from moisture.

2.2 Dosage Information

For the treatment of moderately active ulcerative colitis, the recommended dosage of Mesalamine delayed-release tablets in adults is 1600 mg (two 800 mg tablets) three times daily (total daily dosage of 4.8 grams) for a duration of 6 weeks.

3 DOSAGE FORMS AND STRENGTHS

Mesalamine delayed-release tablets: 800 mg (red-brown, capsule-shaped and imprinted with "WC 800" in black).

4 CONTRAINDICATIONS

Mesalamine delayed-release tablets is contraindicated in patients with known or suspected hypersensitivity to salicylates or aminosalicylates or to any of the ingredients of Mesalamine delayed-release tablets [see Warnings and Precautions (5.3), Adverse Reactions (6.2), and Description (11)].

5 WARNINGS AND PRECAUTIONS

5.1 Renal Impairment

Renal impairment, including minimal change nephropathy, acute and chronic interstitial nephritis, and, rarely, renal failure, has been reported in patients taking products such as Mesalamine delayed-release tablets that contain or are converted to mesalamine [see Adverse Reactions (6.2)].

Evaluate renal function prior to initiation of Mesalamine delayed-release tablets and periodically while on therapy. Evaluate the risks and benefits of using Mesalamine delayed-release tablets in patients with known renal impairment or history of renal disease or taking concomitant nephrotoxic drugs [see Drug Interactions (7.1), Use in Specific Populations (8.6) and Nonclinical Toxicology (13.2)].

5.2 Mesalamine-Induced Acute Intolerance Syndrome

Mesalamine has been associated with an acute intolerance syndrome that may be difficult to distinguish from an exacerbation of ulcerative colitis. Exacerbation of the symptoms of colitis has been reported in 2.3% of Mesalamine delayed-release tablets-treated patients in controlled clinical trials. This acute reaction, characterized by cramping, abdominal pain, bloody diarrhea, and occasionally by fever, headache, malaise, pruritus, rash, and conjunctivitis, has been reported after the initiation of Mesalamine delayed-release tablets as well as other mesalamine products. Symptoms usually abate when Mesalamine delayed-release tablets are discontinued.

5.3 Hypersensitivity Reactions

Hypersensitivity reactions have been reported in patients taking sulfasalazine. Some patients may have a similar reaction to Mesalamine delayed-release tablets or to other compounds that contain or are converted to mesalamine.

As with sulfasalazine, mesalamine-induced hypersensitivity reactions may present as internal organ involvement, including myocarditis, pericarditis, nephritis, hepatitis, pneumonitis, and hematologic abnormalities. Evaluate patients immediately if signs or symptoms of a hypersensitivity reaction are present. Discontinue Mesalamine delayed-release if an alternative etiology for the signs or symptoms cannot be established.

5.4 Hepatic Failure

There have been reports of hepatic failure in patients with pre-existing liver disease who have been administered mesalamine. Caution should be exercised when administering Mesalamine delayed-release tablets to patients with liver impairment.

6 ADVERSE REACTIONS

The most serious adverse reactions seen in Mesalamine delayed-release tablets clinical trials or with other products that contain mesalamine or are metabolized to mesalamine were:

- Renal Impairment [see Warnings and Precautions (5.1)]
- Mesalamine-Induced Acute Intolerance Syndrome [see Warnings and Precautions (5.2)]
- Hypersensitivity Reactions [see Warnings and Precautions (5.3)]
- Hepatic Failure [see Warnings and Precautions (5.4)]

6.1 Clinical Trials Experience

Because clinical trials are conducted under widely varying conditions, adverse reaction rates observed in the clinical trials of a drug cannot be directly compared to rates in the clinical trials of another drug and may not reflect the rates observed in practice.

Mesalamine delayed-release tablets has been evaluated in 896 patients with ulcerative colitis in controlled studies. Three six- week, active-controlled studies were conducted comparing Mesalamine delayed-release tablets 4.8 grams per day with mesalamine-delayed release tablets 2.4 grams per day in patients with mildly to moderately active ulcerative colitis. In these studies, 727 patients were dosed with Mesalamine delayed-release tablets and 732 patients were dosed with mesalamine delayed-release tablets.

The most common reactions reported in the Mesalamine delayed-release tablets group were headache (4.7%), nausea (2.8%), nasopharyngitis (2.5%), abdominal pain (2.3%), diarrhea (1.7%), and dyspepsia (1.7%); Table 1 enumerates adverse reactions that occurred in the three studies. The most common reactions in patients with moderately active ulcerative colitis (602 patients dosed with Mesalamine delayed-release tablets and 618 patients dosed with mesalamine delayed-release 400 mg) were the same as all treated patients.

Discontinuations due to adverse reactions occurred in 3.9% of patients in the Mesalamine delayed-release tablets group and in 4.2% of patients in the mesalamine delayed-release tablet comparator group. The most common cause for discontinuation was gastrointestinal symptoms

associated with ulcerative colitis.

Serious adverse reactions occurred in 0.8% of patients in the Mesalamine delayed-release tablets group and in 1.8% of patients in the mesalamine delayed-release tablet comparator group. The majority involved the gastrointestinal system.

Table 1. Adverse Reactions Occurring in 1 Percent or More of All Treated Patients (Three studies combined)
 | Mesalamine delayed-release 2.4 grams per day | Mesalamine delayed-release tablets
Adverse Reaction | (400 mg Tablet) | 4.8 grams per day (800 mg Tablet)
 | (N = 732) | (N = 727)
Headache | 4.9 % | 4.7 %
Nausea | 2.9 % | 2.8 %
Nasopharyngitis | 1.4 % | 2.5 %
Abdominal pain | 2.3 % | 2.3 %
Diarrhea | 1.9 % | 1.7 %
Dyspepsia | 0.8 % | 1.7 %
Vomiting | 1.6 % | 1.4 %
Flatulence | 0.7 % | 1.2 %
Influenza | 1.2 % | 1.0 %
Pyrexia | 1.2 % | 0.7 %
Cough | 1.4 % | 0.3 %
N = number of patients within specified treatment group
Percent = percentage of patients in category and treatment group
*One Mesalamine delayed-release 800 mg tablet cannot be substituted for two Asacol 400 mg tablets [see Clinical Pharmacology (12.3)].

6.2 Postmarketing Experience

In addition to the adverse reactions reported above in clinical trials involving the Mesalamine delayed-release tablet, the adverse events listed below have been reported in postmarketing experience with other mesalamine-containing products or products that are metabolized to

mesalamine. Because these reactions are reported voluntarily from a population of uncertain size, it is not always possible to reliably estimate their frequency or establish a causal relationship to drug exposure.

Body as a Whole: Facial edema, edema, peripheral edema, asthenia, chills, infection, malaise, pain, neck pain, chest pain, back pain, abdominal enlargement, lupus-like syndrome, drug fever (rare).

Cardiovascular: Pericarditis (rare) and myocarditis (rare) [see Warnings and Precautions (5.3)], pericardial effusion, vasodilation, migraine.

Gastrointestinal: Dry mouth, stomatitis, oral ulcers, anorexia, increased appetite, eructation, pancreatitis, cholecystitis, gastritis, gastroenteritis, gastrointestinal bleeding, perforated peptic ulcer (rare), constipation, hemorrhoids, rectal hemorrhage, bloody diarrhea, tenesmus, stool

abnormality.

Hepatic: There have been rare reports of hepatotoxicity, including jaundice, cholestatic jaundice, hepatitis, and possible hepatocellular damage including liver necrosis and liver failure. Some of these cases were fatal. Asymptomatic elevations of liver enzymes which usually resolve during continued use or with discontinuation of the drug have also been reported. One case of Kawasaki-like syndrome, that included changes in liver enzymes, was also reported [see Warnings and Precautions (5.4)].

Hematologic: Agranulocytosis (rare), aplastic anemia (rare), anemia, thrombocytopenia, leukopenia, eosinophilia, lymphadenopathy.

Musculoskeletal: Gout, rheumatoid arthritis, arthritis, arthralgia, joint disorder, myalgia, hypertonia.

Neurological/Psychiatric: Anxiety, depression, somnolence, insomnia, nervousness, confusion, emotional lability, dizziness, vertigo, tremor, paresthesia, hyperesthesia, peripheral neuropathy (rare), Guillain-Barre syndrome (rare), and transverse myelitis (rare).

Respiratory/Pulmonary: Sinusitis, rhinitis, pharyngitis, asthma exacerbation, pleuritis, bronchitis, eosinophilic pneumonia, interstitial pneumonitis.

Skin: Alopecia, psoriasis (rare), pyoderma gangrenosum (rare), erythema nodosum, acne, dry skin, sweating, pruritus, urticaria, rash.

Special Senses: Ear pain, tinnitus, ear congestion, ear disorder, conjunctivitis, eye pain, blurred vision, vision abnormality, taste perversion.

Renal/Urogenital: Renal failure (rare), interstitial nephritis, minimal change nephropathy [see Warnings and Precautions (5.1)], dysuria, urinary frequency and urgency, hematuria, epididymitis, decreased libido, dysmenorrhea, menorrhagia.

Laboratory Abnormalities: Elevated AST (SGOT) or ALT (SGPT), elevated alkaline phosphatase, elevated GGT, elevated LDH, elevated bilirubin, elevated serum creatinine and BUN.

7 DRUG INTERACTIONS

7.1 Nephrotoxic Agents, Including Non-Steroidal Anti-Inflammatory Drugs

The concurrent use of mesalamine with known nephrotoxic agents, including nonsteroidal anti- inflammatory drugs (NSAIDs) may increase the risk of nephrotoxicity. Monitor patients taking nephrotoxic drugs for changes in renal function and mesalamine-related adverse reactions [seeWarnings and Precautions (5.1)].

7.2 Azathioprine or 6-Mercaptopurine

The concurrent use of mesalamine with azathioprine or 6-mercaptopurine may increase the risk for blood disorders. If concomitant use of Mesalamine delayed-release tablets and azathioprineor 6-mercaptopurine cannot be avoided, monitor blood tests, including complete blood cell counts and platelet counts.

8 USE IN SPECIFIC POPULATIONS

8.1 Pregnancy

Risk Summary

Limited published data on mesalamine use in pregnant women are insufficient to inform a drug-associated risk. No fetal harm was observed in animal reproduction studies of mesalamine in rats and rabbits at oral doses approximately 0.97 times (rat) and 1.95 times (rabbit) the recommended human dose [see Data].

The estimated background risk of major birth defects and miscarriage for the indicated populations is unknown. In the U.S. general population, the estimated background risk of major birth defects and miscarriage in clinically recognized pregnancies is 2 to 4% and 15 to 20%, respectively.

Data

Animal Data

Reproduction studies with mesalamine were performed during organogenesis in rats and rabbits at oral doses up to 480 mg/kg/day. There was no evidence of harm to the fetus. These mesalamine doses were about 0.97 times (rat) and 1.95 times (rabbit) the recommended human dose of 4.8 grams per day, based on body surface area.

8.2 Lactation

Risk Summary

Mesalamine and its N-acetyl metabolite are present in human milk in undetectable to small amounts [see Data]. There are limited reports of diarrhea in breastfed infants. There is no information on the effects of the drug on milk production. The developmental and health benefits of breastfeeding should be considered along with the mother's clinical need for Mesalamine delayed-release tablets and any potential adverse effects on the breastfed infant from the drug or from the underlying maternal condition.

Clinical Considerations

Monitor breastfed infants for diarrhea.

Data

Human Data

In published lactation studies, maternal mesalamine doses from various oral and rectal formulations and products ranged from 500 mg to 3 g daily. The concentration of mesalamine in milk ranged from non-detectable to 0.11 mg/L. The concentration of the N-acetyl-5-aminosalicylic acid metabolite ranged from 5 to 18.1 mg/L. Based on these concentrations, estimated infant daily dosages for an exclusively breastfed infant are 0 to 0.017 mg/kg/day of mesalamine and 0.75 to 2.72 mg/kg/day of N-acetyl-5-aminosalicylic acid.

8.4 Pediatric Use

Safety and effectiveness of Mesalamine delayed-release tablets in pediatric patients have not been established. See the prescribing information for other approved mesalamine products for the safety and effectiveness of these products in pediatric patients.

8.5 Geriatric Use

Clinical studies of Mesalamine delayed-release tablets did not include sufficient numbers of patients aged 65 and over to determine whether they respond differently than younger patients. Reports from uncontrolled clinical studies and postmarketing experience for another oral formulation of mesalamine suggest a higher incidence of blood dyscrasias (agranulocytosis, neutropenia, pancytopenia) in patients who were 65 years or older compared to younger patients. Monitor complete blood cell counts and platelet counts in elderly patients during therapy with

Mesalamine delayed-release tablets.

In general, the greater frequency of decreased hepatic, renal, or cardiac function, and of concomitant disease or other drug therapy in elderly patients should be considered when prescribing Mesalamine delayed-release tablets [see Use in Specific Populations (8.6)].

8.6 Renal Impairment

Mesalamine is known to be substantially excreted by the kidney, and the risk of adverse reactions may be greater in patients with impaired renal function. Evaluate renal function in all patients prior to initiation and periodically while on Mesalamine delayed-release tablets therapy. Monitor patients with known renal impairment or history of renal disease or taking nephrotoxic drugs for decreased renal function and mesalamine-related adverse reactions [see Warnings and Precautions (5.1), Drug Interactions (7.1) and Adverse Reactions (6.2)].

10 OVERDOSAGE

There is no specific antidote for mesalamine overdose and treatment for suspected acute severe toxicity with Mesalamine delayed-release tablets should be symptomatic and supportive. This may include prevention of further gastrointestinal tract absorption, correction of fluid electrolyte imbalance, and maintenance of adequate renal function. Mesalamine delayed-release tablets is a pH dependent delayed-release product and this factor should be considered when treating a suspected overdose.

Single oral doses of 5000 mg/kg mesalamine suspension in mice (approximately 4.2 times the recommended human dose of Mesalamine delayed-release tablets based on body surface area), 4595 mg/kg in rats (approximately 7.8 times the recommended human dose of Mesalamine delayed-release tablets based on body surface area) and 3000 mg/kg in cynomolgus monkeys (approximately 10 times the recommended human dose of Mesalamine delayed-release tablets based on body surface area) were lethal.

11 DESCRIPTION

Each Mesalamine delayed-release tablet for oral administration contains 800 mg of mesalamine, an aminosalicylate. Mesalamine delayed-release tablets have an outer protective coat consisting of a combination of acrylic based resins, Eudragit S (methacrylic acid and methyl methacrylate copolymer (1:2), NF) and Eudragit L (methacrylic acid and methyl methacrylate copolymer (1:1), NF). The inner coat consists of an acrylic based resin, Eudragit S, which dissolves at pH 7

or greater, releasing mesalamine in the terminal ileum and beyond for topical anti- inflammatory action in the colon. Mesalamine (also referred to as 5-aminosalicylic acid or 5-ASA) has the chemical name 5-amino-2-hydroxybenzoic acid; its structural formula is:

Inactive Ingredients: Each tablet contains colloidal silicon dioxide, dibutyl sebacate, edible black ink, ferric oxide red, ferric oxide yellow, lactose monohydrate, magnesium stearate, methacrylic acid and methyl methacrylate copolymer (1:2) (Eudragit S), methacrylic acid and methyl methacrylate copolymer (1:1) (Eudragit L), polyethylene glycol, povidone, sodium starch glycolate, and talc.

12 CLINICAL PHARMACOLOGY

12.1 Mechanism of Action

The mechanism of action of mesalamine is unknown, but appears to be topical rather than systemic. Mucosal production of arachidonic acid metabolites, both through the cyclooxygenase pathways, that is, prostanoids, and through the lipoxygenase pathways, that is, leukotrienes and hydroxyeicosatetraenoic acids, is increased in patients with chronic inflammatory bowel disease, and it is possible that mesalamine diminishes inflammation by blocking cyclooxygenase and inhibiting prostaglandin production in the colon.

12.3 Pharmacokinetics

Absorption

Plasma concentrations of mesalamine (5-aminosalicylic acid; 5-ASA) and its metabolite, N-acetyl-5- aminosalicylic acid (N-Ac-5-ASA) are highly variable following administration of Mesalamine delayed-release tablets. Following single dose oral administration of Mesalamine delayed-release 800 mg tablet in healthy subjects (N = 139) under fasted conditions, the mean Cmax, AUC8-48h and AUC0-tldc values were 208 ng/mL, 2296 ng.h/mL, and 2533 ng.h/mL, respectively. The median [range] Tmax for mesalamine following administration of Mesalamine delayed-release 800 mg tablet was approximately 24 hours [4 to 72 hours], reflecting the delayed-release characteristics of the formulation.

Based on cumulative urinary recovery of mesalamine and N-Ac-5-ASA from single dose studies in healthy subjects, approximately 20% of the orally administered mesalamine in Mesalamine delayed-release tablets is systemically absorbed.

Food Effect: A high calorie (800 to 1000 calories), high fat (approximately 50 % of total caloric content) meal increased mesalamine Cmax by 2.4-fold and mesalamine systemic exposure (AUC8-48 and AUC0-tldc) by 2.8-fold; the median lag-time increased by 8 hours and median tmax by 6 hours (from 24 to 30 hours) [see Dosage and Administration (2.1)].

Comparative exposure between one Mesalamine delayed-release 800 mg tablet and two mesalamine delayed-release 400 mg oral products is unknown [see Dosage and Administration (2.1)].

Elimination

Metabolism

The absorbed mesalamine is acetylated in the gut mucosal wall and by the liver to N-Ac-5-ASA.

Excretion

Absorbed mesalamine is excreted mainly by the kidneys asN-acetyl-5-aminosalicylic acid. Unabsorbed mesalamine is excreted in feces.

13 NONCLINICAL TOXICOLOGY

13.1 Carcinogenesis, Mutagenesis, Impairment of Fertility

Dietary mesalamine was not carcinogenic in rats at doses as high as 480 mg/kg/day, or in mice at 2000 mg/kg/day. These doses are approximately 0.97 and 2.0 times the 4.8 grams per day Mesalamine delayed-release tablet dose (based on body surface area). Mesalamine was not genotoxic in the Ames test, the Chinese hamster ovary cell chromosomal aberration assay, and the mouse micronucleus test. Mesalamine, at oral doses up to 480 mg/kg/day (about 0.97 times the recommended human treatment dose based on body surface area), was found to have no effect on fertility or reproductive performance of male and female rats.

13.2 Animal Toxicology and/or Pharmacology

In animal studies (rats, mice, dogs), the kidney was the principal organ for toxicity. (In the following, comparisons of animal dosing to recommended human dosing are based on body surface area and a 4.8 grams per day dose for a 60 kg person.)

Mesalamine causes renal papillary necrosis in rats at single doses of approximately 750 mg/kg to 1000 mg/kg (1.5 to 2.0 times the recommended human dose). Doses of 170 and 360 mg/kg/day (about 0.3 and 0.73 times the recommended human dose) given to rats for six months produced papillary necrosis, papillary edema, tubular degeneration, tubular mineralization, and urothelial hyperplasia.

In mice, oral doses of 4000 mg/kg/day (approximately 4.1 times the recommended human dose) for three months produced tubular nephrosis, multifocal/diffuse tubulo-interstitial inflammation, and multifocal/diffuse papillary necrosis.

In dogs, single doses of 6000 mg (approximately 6.25 times the recommended human dose) of delayed- release mesalamine tablets resulted in renal papillary necrosis but were not fatal. Renal changes have occurred in dogs given chronic administration of mesalamine at doses of 80 mg/kg/day (0.5 times the recommended human dose).

14 CLINICAL STUDIES

14.1 Moderately Active Ulcerative Colitis

The efficacy of Mesalamine delayed-release tablets at 4.8 grams per day was studied in a six-week, randomized, double-blind, active-controlled study in 772 patients with moderately active ulcerative colitis (UC). Moderately active UC was defined as a Physician's Global Assessment

(PGA) score of 2; the PGA is a four-point scale (0 to 3) that encompasses the clinical assessments of rectal bleeding, stool frequency, and sigmoidoscopy findings.

Patients were randomized 1:1 to the Mesalamine delayed-release tablets 4.8 grams per day group (two Mesalamine delayed-release tablets three times a day) or the mesalamine delayed-release 2.4 grams per day group (two mesalamine delayed-release 400 mg tablets three times a day).

Patients characteristically had a history of previous use of oral 5-ASAs (86%), steroids (41%), and rectal therapies (49%), and demonstrated clinical symptoms of three or more stools over normal per day (87%) and obvious blood in the stool most or all of the time (70%). The study

population was primarily Caucasian (97%), had a mean age of 43 years (8% aged 65 years or older), and included slightly more males (56%) than females (44%).

The primary endpoint was treatment success defined as improvement from baseline to Week 6 based on the PGA. Treatment success rates were similar in the two groups: 70% in the Mesalamine delayed-release tablets group and 66% in the Asacol group (difference: 5%; 95% CI: [-1.9%, 11.2%]).

A second controlled study supported the efficacy of Mesalamine delayed-release tablets at 4.8 grams per day. Treatment success was 72% in patients with moderately active UC treated with Mesalamine delayed-release tablets.

16 HOW SUPPLIED/STORAGE AND HANDLING

Product: 50090-3497

NDC: 50090-3497-0 180 TABLET, DELAYED RELEASE in a BOTTLE

17 PATIENT COUNSELING INFORMATION

Administration [see Dosage and Administration (2.1)]

- Inform patients that if they are switching from a previous oral mesalamine therapy to Mesalamine delayed-release tablets to discontinue their previous oral mesalamine therapy and follow the dosing instructions for Mesalamine delayed-release tablets. One Mesalamine delayed-release 800 mg tablet is not substitutable for two mesalamine delayed-release 400 mg oral products.
- Inform patients to take Mesalamine delayed-release tablets on an empty stomach, at least 1 hour before and 2 hours after a meal.
- Instruct patients to swallow the Mesalamine delayed-release tablets whole, taking care not to break, cut, or chew the tablets, because the coating is an important part of the delayed-release formulation.
- Inform patients that intact, partially intact, and/or tablet shells have been reported in the stool. Instruct patients to contact their physician if this occurs repeatedly.
- Instruct patients to protect Mesalamine delayed-release tablets from moisture.

Renal Impairment

- Inform patients that Mesalamine delayed-release tablets may decrease their renal function, especially if they have known renal impairment or are taking nephrotoxic drugs, and periodic monitoring of renal function will be performed while they are on therapy. Advise patients to complete all blood tests ordered by their physician [see Warnings and Precautions (5.1)].

Mesalamine-Induced Acute Intolerance Syndrome

- Instruct patients to report to their physician if they experience new or worsening symptoms of cramping, abdominal pain, bloody diarrhea, and sometimes fever, headache, and rash [see Warnings and Precautions (5.2)] .

Hypersensitivity Reactions

- Inform patients of the signs and symptoms of hypersensitivity reactions, and advise them seek immediate medical care should signs and symptoms occur [see Warnings and Precautions (5.3)] .

Hepatic Failure

- Inform patients with known liver disease of the signs and symptoms of worsening liver function and advise them to report to their physician if they experience such signs or symptoms [see Warnings and Precautions (5.4)].

Blood Disorders

- Inform elderly patients and those taking azathioprine or 6-mercaptopurine of the risk for blood disorders and the need for periodic monitoring of complete blood cell counts and platelet counts while on therapy. Advise patients to complete all blood tests ordered by their physician [see Drug Interactions (7.2), Use in Specific Populations (8.5)] .

Distributed By:

Zydus Pharmaceuticals USA Inc.

Pennington, NJ 08534

AsacolR is a registered trademark of Medeva Pharma Suisse AG, licensed

to Allergan Pharmaceuticals International Limited.

© 2016 Allergan. All rights reserved.

storage

Store and dispense in the original bottle, protect from moisture, and keep the bottle tightly closed. Do not remove desiccant pouch (silica gel) from bottle. Store at controlled room temperature, 20° to 25° C (68° to 77° F); excursions are permitted 15° to 30° C (59° to 86° F). [See USP Controlled Room Temperature]